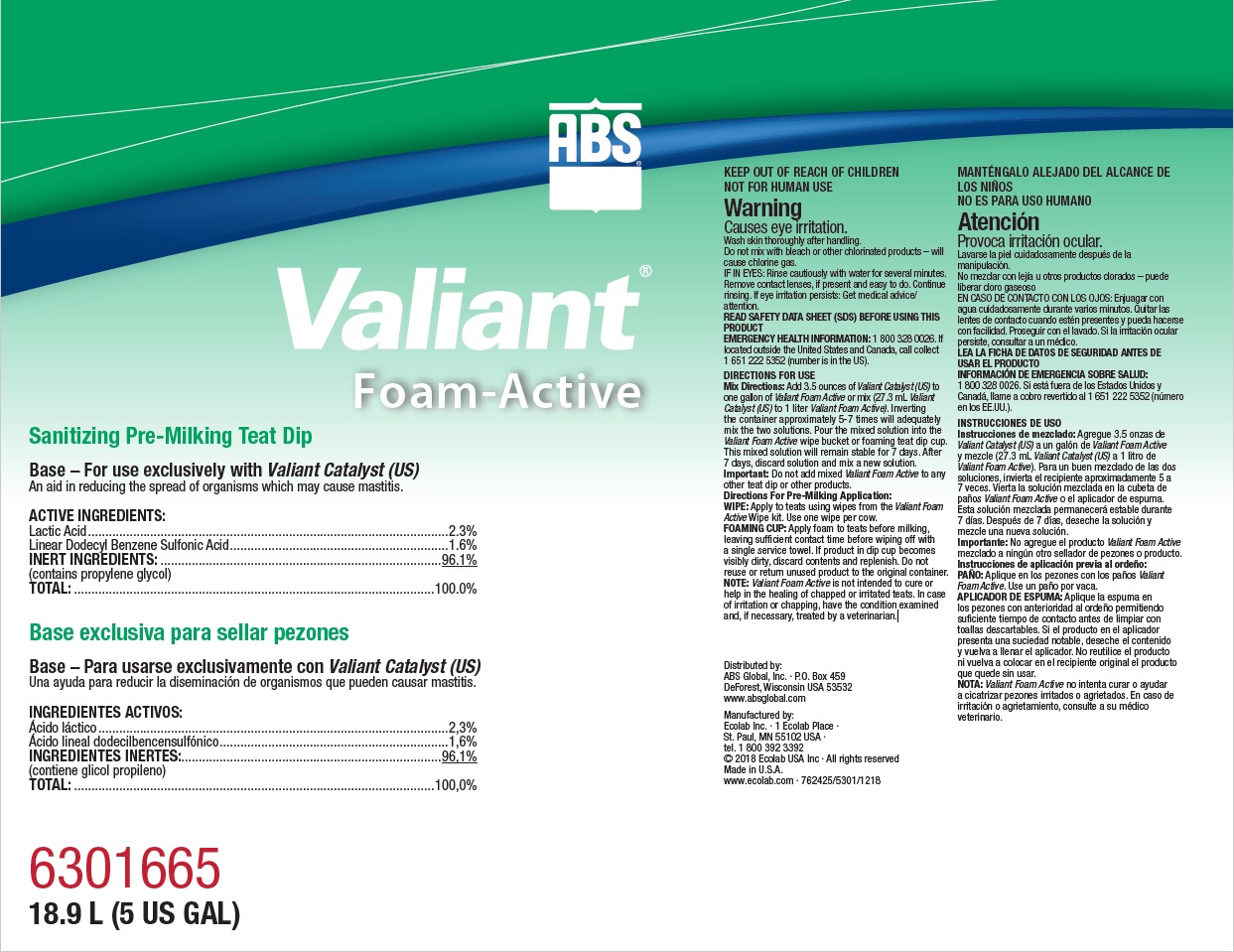 DRUG LABEL: VALIANT
NDC: 59282-113 | Form: SOLUTION
Manufacturer: ABS Global Inc.
Category: animal | Type: OTC ANIMAL DRUG LABEL
Date: 20190624

ACTIVE INGREDIENTS: LACTIC ACID 23 mg/1 mL; DODECYLBENZENESULFONIC ACID 16 mg/1 mL
INACTIVE INGREDIENTS: Water; PROPYLENE GLYCOL

KEEP OUT OF REACH OF CHILDREN

NOT FOR HUMAN USE

Warning

Causes eye irritation.

Wash skin thoroughly after handling.

Do not mix with bleach or other chlorinated products – will

cause chlorine gas.

VETERINARY INDICATIONS

DIRECTIONS FOR USE

Mix Directions: Add 3.5 ounces of Valiant Catalyst (US) to

one gallon of Valiant Foam Active or mix (27.3 mL Valiant

Catalyst (US) to 1 liter Valiant Foam Active). Inverting

the container approximately 5-7 times will adequately

mix the two solutions. Pour the mixed solution into the

Valiant Foam Active wipe bucket or foaming teat dip cup.

This mixed solution will remain stable for 7 days. After

7 days, discard solution and mix a new solution.

Important: Do not add mixed Valiant Foam Active to any

other teat dip or other products.

Directions For Pre-Milking Application:

WIPE: Apply to teats using wipes from the Valiant Foam

Active Wipe kit. Use one wipe per cow.

FOAMING CUP: Apply foam to teats before milking,

leaving sufficient contact time before wiping off with

a single service towel. If product in dip cup becomes

visibly dirty, discard contents and replenish. Do not

reuse or return unused product to the original container.

NOTE: Valiant Foam Active is not intended to cure or

help in the healing of chapped or irritated teats. In case

of irritation or chapping, have the condition examined

and, if necessary, treated by a veterinarian.

OTHER SAFETY INFORMATION

IF IN EYES: Rinse cautiously with water for several minutes.

Remove contact lenses, if present and easy to do. Continue

rinsing. If eye irritation persists: Get medical advice/

attention.

READ SAFETY DATA SHEET (SDS) BEFORE USING THIS

PRODUCT

EMERGENCY HEALTH INFORMATION: 1 800 328 0026. If

located outside the United States and Canada, call collect

1 651 222 5352 (number is in the US).

Principal display panel and representative label

ABS

Valiant

Foam-Active

Sanitizing Pre-Milking Teat Dip

Base – For use exclusively with Valiant Catalyst (US)

An aid in reducing the spread of organisms which may cause mastitis.

ACTIVE INGREDIENTS:

Lactic Acid.........................................................................................................2.3%

Linear Dodecyl Benzene Sulfonic Acid................................................................1.6%

INERT INGREDIENTS:..................................................................................96.1%

(contains propylene glycol)

TOTAL:.........................................................................................................100.0%

6301665

18.9 L (5 US GAL)

Distributed by:

ABS Global, Inc. ∙ P.O. Box 459

DeForest, Wisconsin USA 53532

www.absglobal.com

Manufactured by:

Ecolab Inc. ∙ 1 Ecolab Place ∙

St. Paul, MN 55102 USA ∙

tel. 1 800 392 3392

© 2018 Ecolab USA Inc ∙ All rights reserved

Made in U.S.A.

www.ecolab.com ∙ 762425/5301/1218